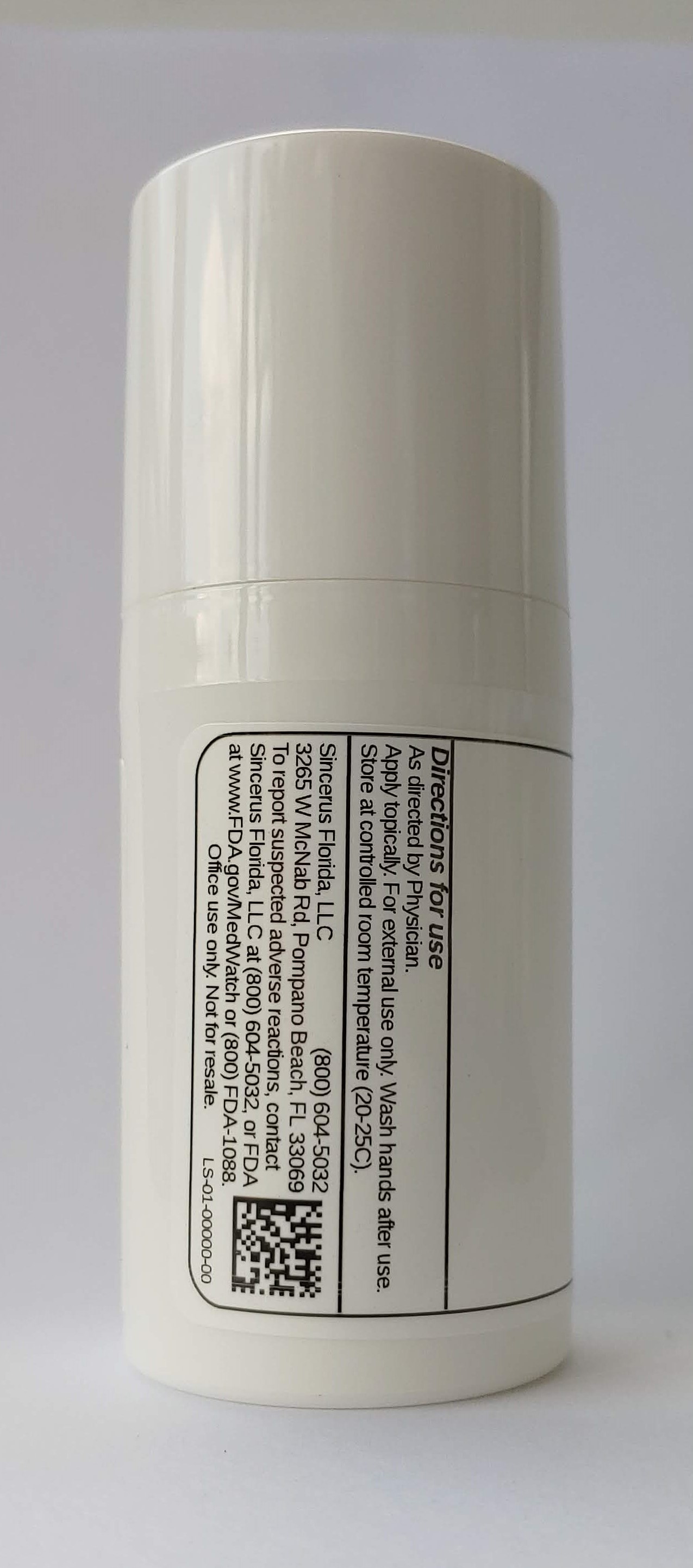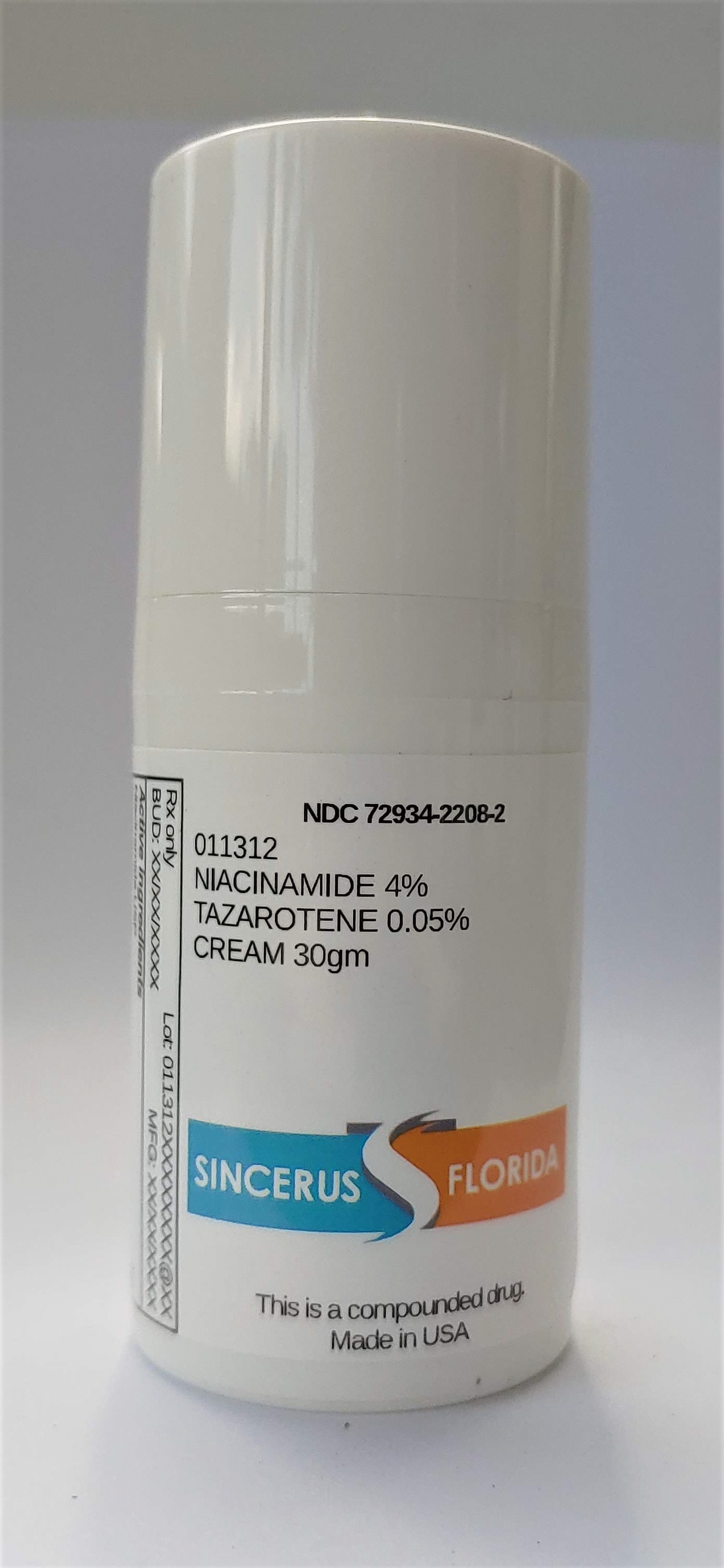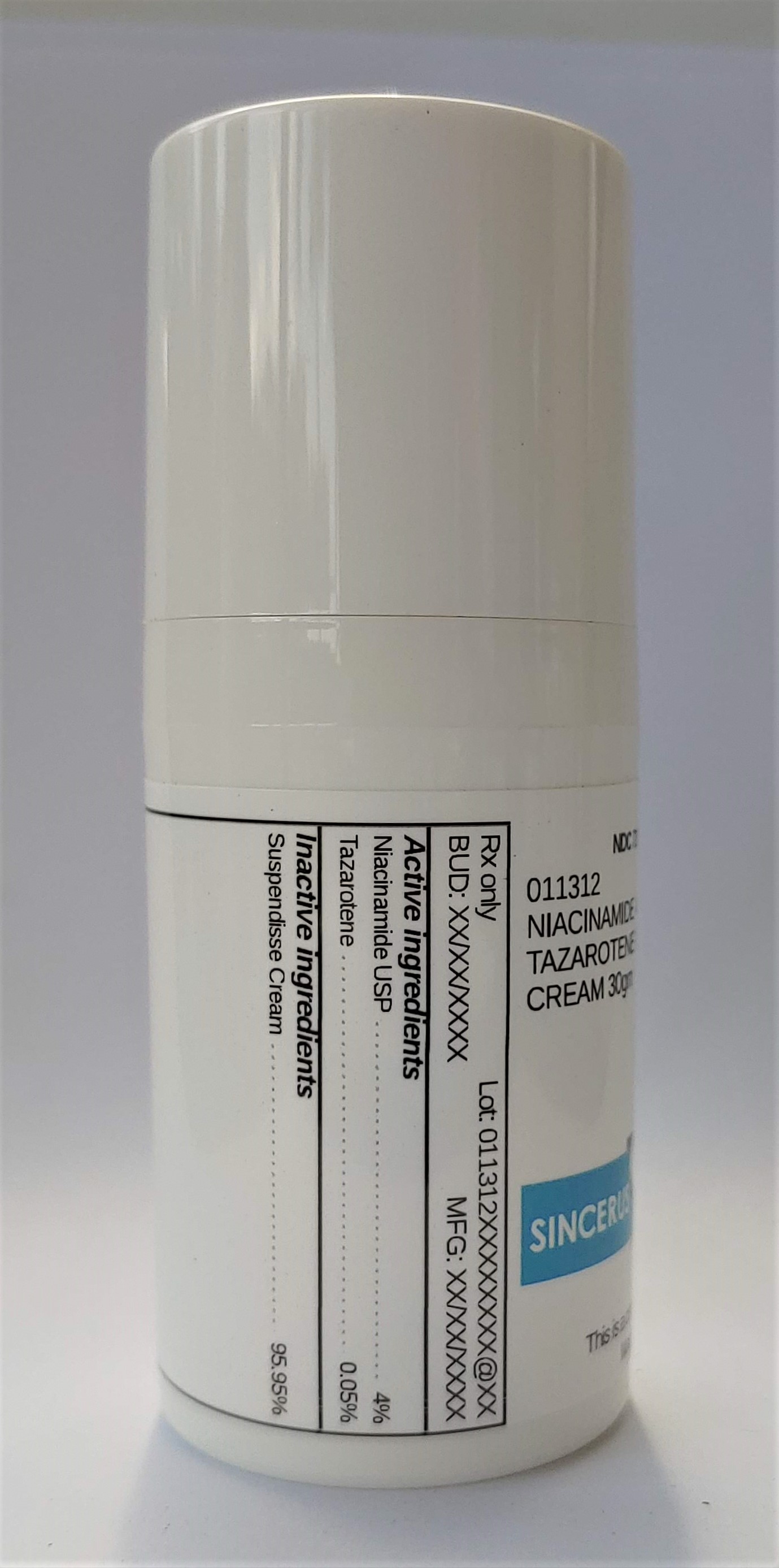 DRUG LABEL: 011312 NIACINAMIDE 4% / TAZAROTENE 0.05%
NDC: 72934-2208 | Form: CREAM
Manufacturer: Sincerus Florida, LLC
Category: prescription | Type: HUMAN PRESCRIPTION DRUG LABEL
Date: 20200702

ACTIVE INGREDIENTS: TAZAROTENE 0.05 g/100 g; NIACINAMIDE 4 g/100 g

011312 NIACINAMIDE 4% / TAZAROTENE 0.05%